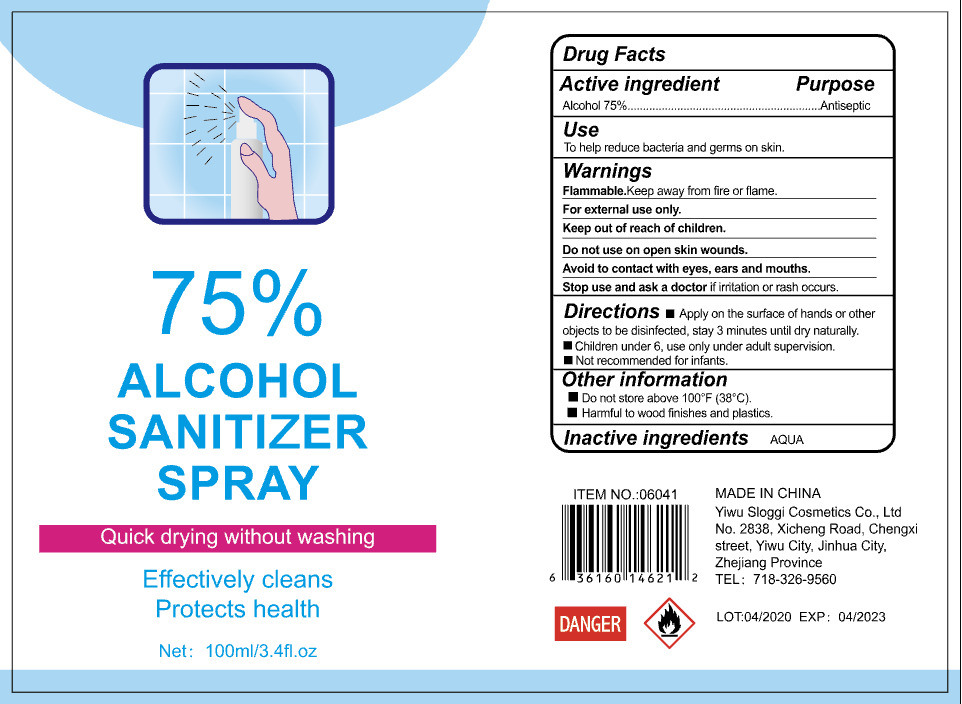 DRUG LABEL: alcohol sanitizerspray
NDC: 54225-006 | Form: LIQUID
Manufacturer: YIWU SLOGGI COSMETICS CO.,LTD
Category: otc | Type: HUMAN OTC DRUG LABEL
Date: 20200513

ACTIVE INGREDIENTS: ALCOHOL 75 mL/100 mL
INACTIVE INGREDIENTS: WATER

DOSAGE AND ADMINISTRATION

Do not store above 100°F (38°C)

INACTIVE INGREDIENT

AQUA

INDICATIONS AND USAGE

Apply on the surface of hands or other objects to be disinfected, stay 3 minutes until dry naturally.

ACTIVE INGREDIENT

ALCOHOL

keep out of reach of children

PURPOSE

Disinfection
Sterilization

WARNINGS

Flammable.Keep away from fire or flame.For external use only.Keep out of reach of children.Do not use on open skin wounds.Avoid to contact with eyes, ears and mouths.Stop use and ask a doctor if iritation or rash occurs.